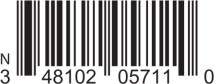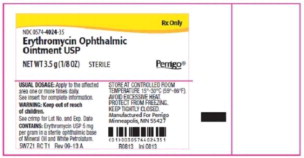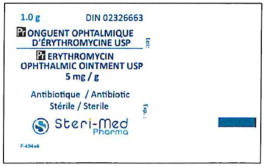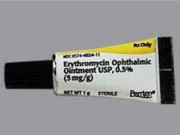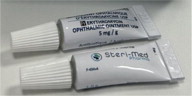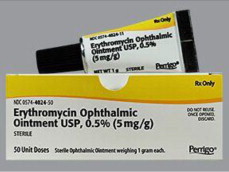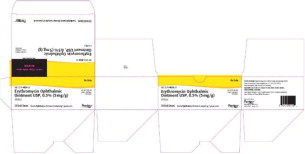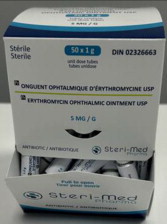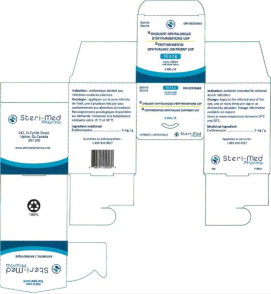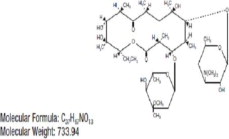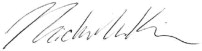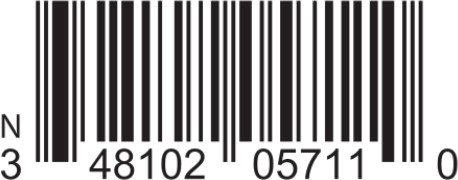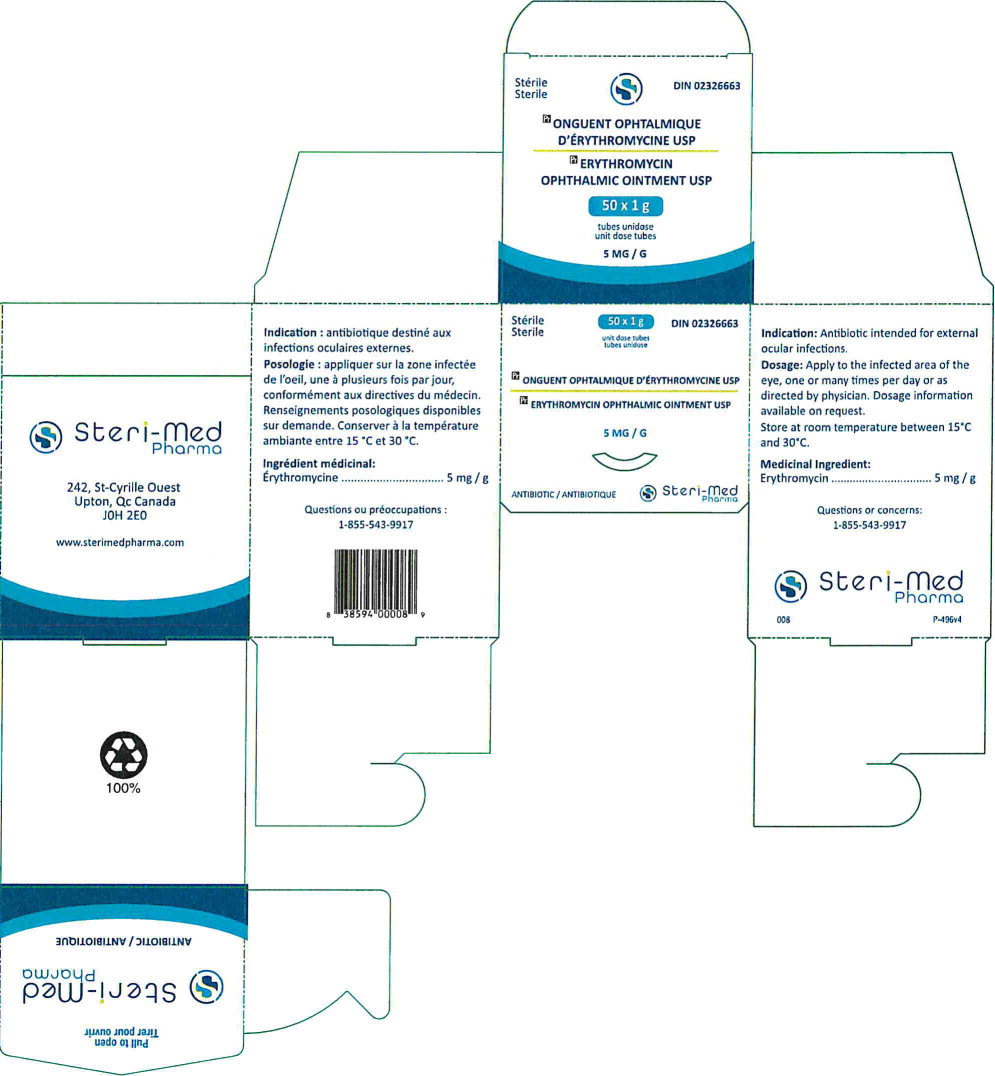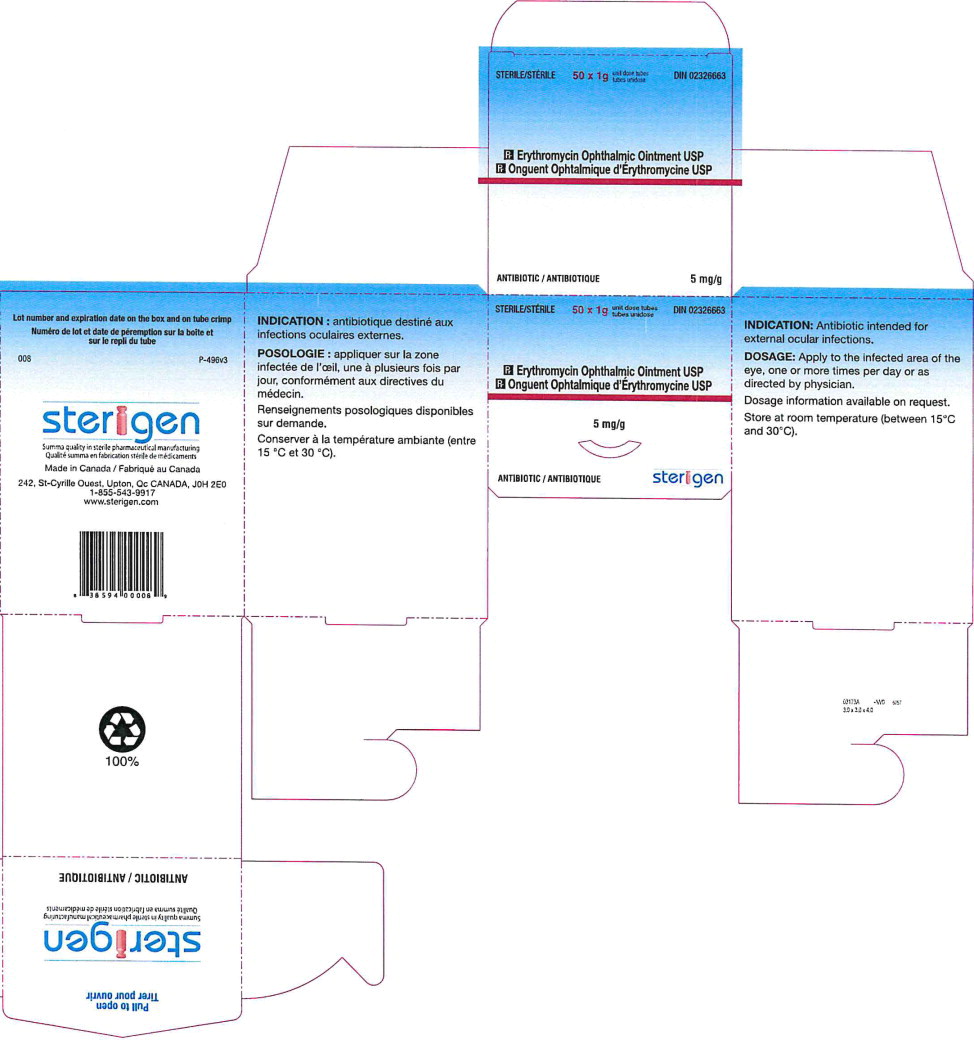 DRUG LABEL: Erythromycin
NDC: 48102-057 | Form: OINTMENT
Manufacturer: Fera Pharmaceuticals, LLC
Category: prescription | Type: HUMAN PRESCRIPTION DRUG LABEL
Date: 20231026

ACTIVE INGREDIENTS: ERYTHROMYCIN 5 mg/1 g
INACTIVE INGREDIENTS: MINERAL OIL; PETROLATUM

HEALTH CARE PROVIDER LETTER

January 9, 2024

IMPORTANT PRESCRIBING INFORMATION

Subject:

Temporary Importation of Steri-Med Pharma, Inc.'s Erythromycin Ophthalmic Ointment 5mg/g to Address Drug Shortage

Dear Healthcare Provider,

In order to address the current drug shortage of Erythromycin Ophthalmic Ointment, Fera Pharmaceuticals, LLC (Fera), in conjunction with Steri-Med Pharma, Inc. (Steri-Med), is coordinating with the U.S. FDA Drug Shortage Staff to increase its availability in the U.S. market by temporary importation of non-FDA approved product from Canada. Effective immediately and during this temporary period, Fera will distribute the following product:

Table 1: Imported Product Information
Product Name and Description | Size | Drug Identification Number (DIN) | National Drug Code (NDC)
Erythromycin Ophthalmic Ointment USP, 5 mg/g | 1 g Tube | 02326663 | 48102-057-11
 |  |  | The linear barcode on the imported product may not register accurately on U.S. scanning systems. A linear NDC barcode is provided above to assist with input by U.S. scanning system.

This supply of Erythromycin Ophthalmic Ointment is approved and marketed in Canada, under DIN 02326663, and manufactured by Steri-Med (previously known as Sterigen), a facility licensed by Health Canada. At this time, no other entity except Steri-Med or its distributor Fera is authorized by the FDA to import or distribute Steri-Med's Erythromycin Ophthalmic Ointment in the U.S.

It is important to note the following:

- The strength and qualitative composition of the imported drug product are the same as the FDA- approved drug product. Both also meet the USP monograph specification.
- The linear barcode on the imported product label may not register accurately on U.S. scanning systems. Institutions should manually input the product information into their systems to confirm that barcode systems do not provide incorrect information when the product is scanned. Alternative procedures should be followed to assure that the correct drug product is being used and administered to individual patients. The linear barcode is provided in the Table 1 above and Appendix 1 to assist with input of product information in the institutional setting.
  In addition, the carton of the imported product does not include a product identifier as required under the Drug Supply Chain Security Act (DSCSA). Specifically, each package does not include the NDC, unique serial number, lot number, and expiration date in both human-readable and a two-dimensional data matrix barcode. Additionally, the imported product may not be accompanied with DSCSA product tracing documentation (transaction information, transaction history, and transaction statement).
- The drug product being distributed by Fera Pharmaceuticals, LLC is approved in Canada. The Prescribing Information (PI) and Patient Medication Information (Medication Guide) reviewed and approved by Health Canada differ from the full prescribing information for the current U.S. FDA Reference Standard (RS). The U.S. FDA label does not contain a Medication Guide.
  In particular, the FDA label provides more detailed information regarding DESCRIPTION, CLINICAL PHARMACOLOGY, USAGE during pregnancy and in infants, and in PRECAUTIONS.
  Please refer to the package insert for the U.S. FDA-approved Erythromycin Ophthalmic Ointment USP, 5 mg/g for full prescribing information.

Table 2. Comparison Between the FDA-approved vs. Steri-Med Carton and Tube Labels
 | FDA-approved Product Labels | Imported Product Labels from Steri-Med (formerly Sterigen)*
Tube
Carton

Table 3. Comparison Between the FDA-approved vs. Steri-Med Prescribing Information
PACKAGE INSERT SECTION | FDA-Approved RS Label | Steri-Med Label
DESCRIPTION | Erythromycin Ophthalmic Ointment belongs to the macrolide group of antibiotics. It is basic and readily forms a salt when combined with an acid. The base, as crystals or powder, is slightly soluble in water, moderately soluble in ether, and readily soluble in alcohol or chloroform. Erythromycin ((3R*,4S*,5S*,6R*,7R*,9R*,11R*,12R*,13S*,14R*)- 4-[(2,6-dideoxy-3-C-methyl-3-0-methyl-α-L-ribo-hexopyranosyl)oxy]-14-ethyl-7,12,13-trihydroxy-3,5,7,9,11,13-hexamethyl-6-[[3,4,6-trideoxy-3-(dimethylamino)-ß-D-xylo-hexopyranosyl]oxy]oxacyclotetradecane-2,10-dione) is antibiotic produced from a strain of Streptomyces erythraeus. It has the following structural formula: Each gram contains Erythromycin USP 5 mg in a sterile ophthalmic base of mineral oil and white petrolatum. | THERAPEUTIC CLASSIFICATION Antibiotic
CLINICAL PHARMACOLOGY | Microbiology Erythromycin inhibits protein synthesis without affecting nucleic acid synthesis. Erythromycin is usually active against the following organisms in vitro and in clinical infections: Streptococcus pyogenes (group A ß-hemolytic) Alpha-hemolytic streptococci (viridans group) Staphylococcus aureus, including penicillinase-producing strains (methicillin-resistant staphylococci are uniformly resistant to erythromycin) Streptococcus pneumonia Mycoplasma pneumoniae (Eaton Agent, PPLO) Haemophilus influenzae (not all strains of this organism are susceptible at the erythromycin concentrations ordinarily achieved) Treponema pallidum Corynebacterium diphtheriae Neisseria gonorrhoeae Chlamydia trachomatis | Erythromycin inhibits protein synthesis by binding to the 50S ribosomal subunit within the microorganism. It is usually bacteriostatic but may be bactericidal depending on the sensitivity and number of organisms and the concentrations of the drug. Its spectrum of activity is similar to that of penicillin G. Resistance to erythromycin of some strains of H. influenza and Staphylococci has been demonstrated.
INDICATIONS AND USAGE | For the treatment of superficial ocular infections involving the conjunctiva and/or cornea caused by organisms susceptible to erythromycin. For prophylaxis of ophthalmia neonatorum due to N. gonorrhoeae or C. trachomatis. The effectiveness of erythromycin in the prevention of ophthalmia caused by penicillinase-producing N. gonorrheae is not established. For infants born to mothers with clinically apparent gonorrhea, intravenous or intramuscular injections of aqueous crystalline penicillin G should be given; a single dose of 50,000 units for term infants or 20,000 units for infants of low birth weight. Topical prophylaxis alone is inadequate for these infants. | For the treatment of superficial ocular infections involving the conjunctiva and/or cornea caused by organisms susceptible to erythromycin. For prophylaxis of ophthalmic neonatorum due to N. gonorrhoeae or C. trachomatis. The Canadian Pediatric Society, the Centers for Diseases Control and the Committee on Drugs (US), the Committee of Fetus and Newborn and the Committee on Infectious Diseases of the American Academy of Pediatrics recommend 1% silver nitrate solution in single dose ampoules or single use tubes of an ophthalmic ointment containing 0.5% erythromycin or 1% tetracycline as effective and acceptable regimens for prophylaxis of gonococcal ophthalmia neonatorum. Erythromycin ophthalmic ointment has also been effective for prevention of neonatal conjunctivitis due to C. trachomatis, a condition that may develop one to several weeks after delivery in infants of mothers whose birth canal harbor the organism. To reduce the development of drug-resistant bacteria and maintain the effectiveness of ERYTHROMYCIN ophthalmic ointment and other antibacterial drugs, ERYTHROMYCIN ophthalmic ointment should be used only to treat infections that are proven or strongly suspected to be caused by susceptible bacteria. When culture and susceptibility information are available, they should be considered in selecting or modifying antibacterial therapy. In the absence of such data, local epidemiology and susceptibility patterns may contribute to the empiric selection of therapy.
CONTRAINDICATIONS: | This drug is contraindicated in patients with a history of hypersensitivity to erythromycin. | Erythromycin and its derivatives should not be used in patients with known hypersensitivity to these drugs or any ingredient in the formulations or with infections that are resistant to the drug (primarily certain Staphylococci organisms).
PRECAUTIONS | General: The use of antimicrobial agents may be associated with the overgrowth of nonsusceptible organisms including fungi; in such a case, antibiotic administration should be stopped and appropriate measures taken. Information for Patients: Avoid contaminating the applicator tip with material from the eye, fingers, or other source. Carcinogenesis, Mutagenesis, Impairment of Fertility: Two year oral studies conducted in rats with erythromycin did not provide evidence of tumorigenicity. Mutagenicity studies have not been conducted. No evidence of impaired fertility that appeared related to erythromycin was reported in animal studies. Pregnancy: Teratogenic effects Pregnancy Category B. Reproduction studies have been performed in rats, mice, and rabbits using erythromycin and its various salts and esters, at doses that were several multiples of the usual human dose. No evidence of harm to the fetus that appeared related to erythromycin was reported in these studies. There are, however, no adequate and well controlled studies in pregnant women. Because animal reproductive studies are not always predictive of human response, the erythromycins should be used during pregnancy only if clearly needed. Nursing Mothers: Caution should be exercised when erythromycin is administered to a nursing woman. Pediatric Use: See INDICATIONS AND USAGE and DOSAGE AND ADMINISTRATION. | WARNINGS AND PRECAUTIONS Susceptibility/Resistance Prescribing ERYTHROMYCIN ophthalmic ointment in the absence of a proven or strongly suspected bacterial infection is unlikely to provide benefit to the patient and risks the development of drug-resistant bacteria. The rare possibility of superinfection caused by overgrowth of non-susceptible bacteria or fungi should be kept in mind during prolonged or repeated therapy, especially when other antibacterial agents are simultaneously employed. In such instances the drug should be withdrawn and appropriate treatment instituted if necessary.
ADVERSE REACTIONS | The most frequently reported adverse reactions are minor ocular irritations, redness, and hypersensitivity reactions. To report SUSPECTED ADVERSE REACTIONS, contact Perrigo at 1-866-634-9120 or FDA at 1-800-FDA-1088 or www.fda.gov/medwatch. | ADVERSE EFFECTS Serious allergic reactions to erythromycin have been extremely infrequent. Mild allergic reactions, such as urticaria and morbilliform skin rashes have occurred. Should a patient demonstrate signs of hypersensitivity, administer appropriate countermeasures such as epinephrine, corticosteroid and antihistamines, and withdraw the antibiotic.
DOSAGE AND ADMINISTRATION | In the treatment of superficial ocular infections, a ribbon approximately 1 cm in length of Erythromycin Ophthalmic Ointment should be applied directly to the infected structure up to 6 times daily, depending on the severity of the infection. For prophylaxis of neonatal gonococcal or chlamydial conjunctivitis, a ribbon of ointment approximately 1 cm in length should be instilled into each lower conjunctival sac. The ointment should not be flushed from the eye following instillation. A new tube should be used for each infant. | In the treatment of external ocular infections, apply the ointment directly to the infected structure one or more times daily, depending on the severity of the infection. For prophylaxis neonatal gonococcal or chlamydial conjunctivitis, a ribbon of ointment approximately 0.5 to 1 cm in length should be instilled into each conjunctival sac. The ointment should not be flushed from the eye following installation. A new tube should be used for each infant. Infants born by cesarean section as well as those delivered by vaginal route should receive prophylaxis.

To order, please call (414) 434-6604. For additional questions about the information contained in this letter, please contact Fera at (516) 277-1449.

Healthcare providers and patients are encouraged to report adverse events in patients using imported Erythromycin Ophthalmic Ointment to Fera at (414) 434-6604.

Adverse events or quality problems experienced with the use of this product may also be reported to the FDA's MedWatch Adverse Event Reporting Program either online, by regular mail, or by fax:

- Complete and submit the report Online: www.fda.gov/medwatch/report.htm
- Regular mail or Fax: Download form www.fda.gov/MedWatch/getforms.htm or call 1-800-332-1088 to request a reporting form, then complete and return to the address on the pre-addressed form or submit by fax to 1-800-FDA-0178 (1-800-332-0178).

Sincerely,

Michelle Kim, PharmD.

Sr. Director of Regulatory Affairs

Appendix 1: Linear Barcode for U.S. NDC Scanning
Product Name | Erythromycin Ophthalmic Ointment USP, 5 mg/g
Manufacturer | Steri-Med Pharma, Inc. (formerly Sterigen)
Size | 1 g Tube
NDC | 48102-057-11
Linear Barcode

Principal Display Panel - 5 mg Carton Label (Steri-Med)

Sterile
Sterile

50 x 1g

unit dose tubes
tubes unidose

DIN 02326663

Pr ONGUENT OPHTALMIQUE D'ERYTHROMYCINE USP

Pr ERYTHROMYCIN OPHTHALMIC OINTMENT USP

5 MG/G

ANTIBIOTIC / ANTIBIOTIQUE

Steri-Med
Pharma

Principal Display Panel - 5 mg Carton Label (Sterigen)

STERILE/STERILE

50 x 1g

unit dose tubes
tubes unidose

DIN 02326663

Pr Erythromycin Ophthalmic Ointment USP

Pr Onguent Ophtalmique d'Erythromycine USP

5 mg/g

ANTIBIOTIC / ANTIBIOTIQUE

sterigen